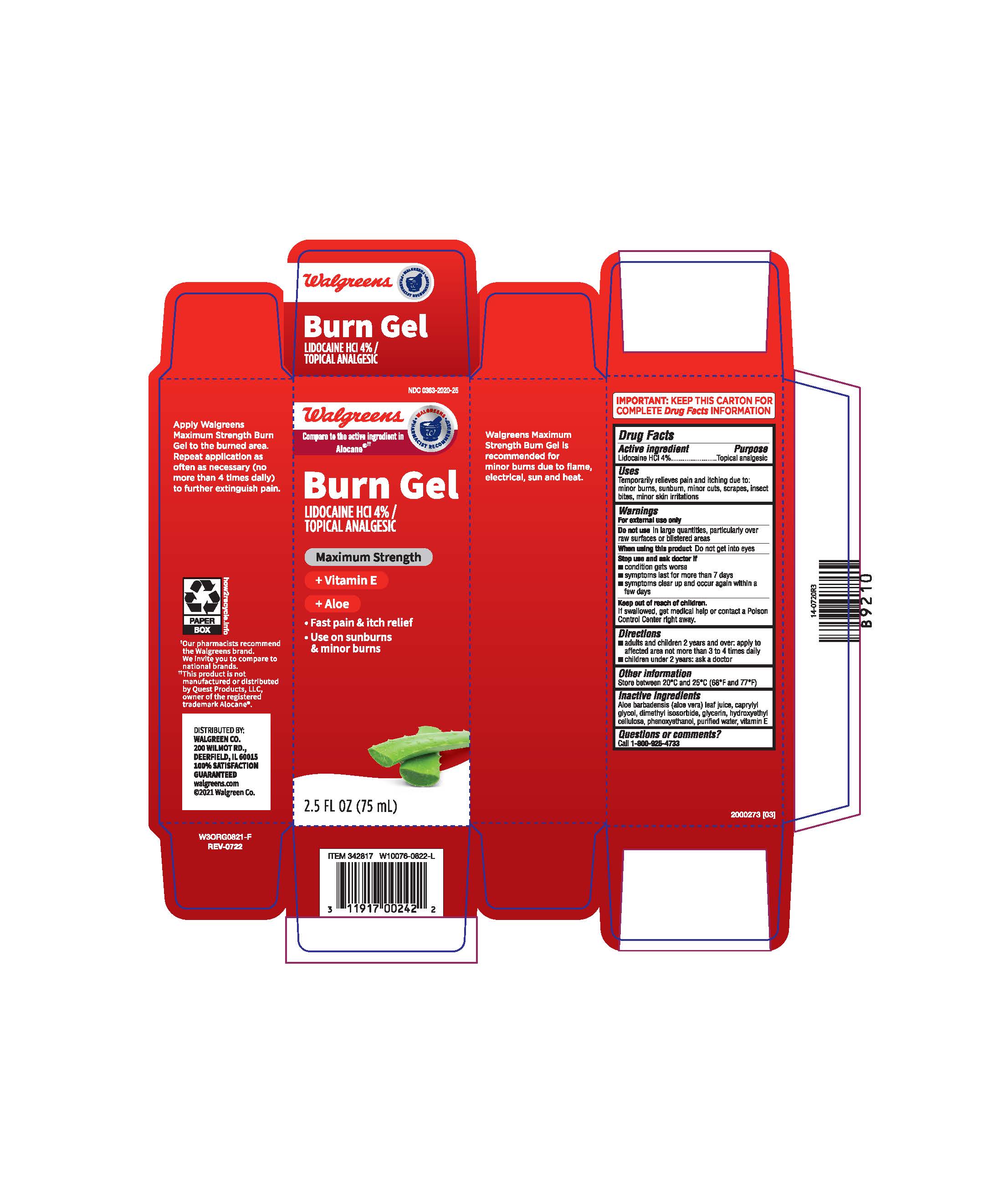 DRUG LABEL: WALGREENS BURN
NDC: 0363-2020 | Form: GEL
Manufacturer: WALGREENS
Category: otc | Type: HUMAN OTC DRUG LABEL
Date: 20251229

ACTIVE INGREDIENTS: LIDOCAINE HYDROCHLORIDE 4 g/100 g
INACTIVE INGREDIENTS: HYDROXYETHYL CELLULOSE, UNSPECIFIED; .ALPHA.-TOCOPHEROL ACETATE; PHENOXYETHANOL; GLYCERIN; CAPRYLYL GLYCOL; DIMETHYL ISOSORBIDE; WATER; ALOE VERA LEAF

Walgreens Burn Gel

Active Ingredient

Lidocaine HCl 4%

Purpose

Topical analgesic

Uses

Temporarily relieves pain and itching due to: minor burns, sunburn, minor cuts, scrapes, insect bites, minor skin irritations

Warnings

For external use only

Do Not Use

In large quantities, particularly over raw surfaces or blistered areas

When Using This Product

Do not get into eyes

Stop use and ask doctor if

condition gets worse

symptoms last for more than 7 days

symptoms clear up and occur again within a few days

Keep out of reach of children

Keep out of reach of children

If swallowed, get medical help or contact a Poison Control Center right away.

Directions

- adults and children 2 years and over: apply to affected area not more than 3 to 4 times daily

- children under 2 years: ask a doctor

Other information

Store between 20 °C and 25 °C (68 °F and 77 °F)

Inactive Ingredients

Aloe barbadensis (aloe vera) leaf juice, caprylyl glycol, dimethyl isosorbide, glycerin, hydroxyethyl cellulose, phenoxyethanol, purified water, vitamin E